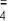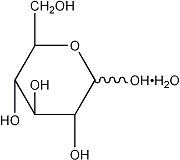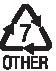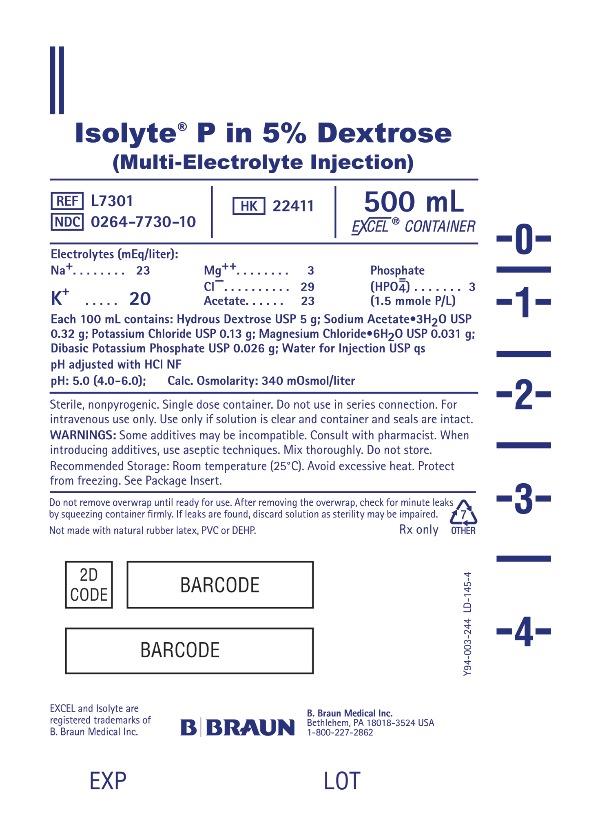 DRUG LABEL: Isolyte P in Dextrose
NDC: 0264-7730 | Form: INJECTION, SOLUTION
Manufacturer: B. Braun Medical Inc.
Category: prescription | Type: HUMAN PRESCRIPTION DRUG LABEL
Date: 20240624

ACTIVE INGREDIENTS: DEXTROSE MONOHYDRATE 5 g/100 mL; SODIUM ACETATE 0.32 g/100 mL; POTASSIUM CHLORIDE 0.13 g/100 mL; MAGNESIUM CHLORIDE 0.031 g/100 mL; POTASSIUM PHOSPHATE, DIBASIC 0.026 g/100 mL
INACTIVE INGREDIENTS: WATER; HYDROCHLORIC ACID

Isolyte® P in 5% Dextrose (Multi-Electrolyte Injection)

DESCRIPTION

Each 100 mL of Isolyte® P (Multi-Electrolyte Injection) in 5% Dextrose contains:
Hydrous Dextrose USP 5 g; Sodium Acetate Trihydrate USP 0.32 g
Potassium Chloride USP 0.13 g; Magnesium Chloride Hexahydrate USP 0.031 g
Dibasic Potassium Phosphate USP 0.026 g; Water for Injection USP qs

pH adjusted with Hydrochloric Acid NF
pH: 5.0 (4.0–6.0) Calories per liter: 170
Calculated Osmolarity: 340 mOsmol/liter

Concentration of Electrolytes (mEq/liter): Sodium 23; Chloride 29
Acetate (CH3COO^-) 23; Potassium 20; Magnesium 3; [1.5 mmole P/liter] Phosphate (HPO) 3

Isolyte® P in 5% Dextrose is sterile, nonpyrogenic, and contains no bacteriostatic or antimicrobial agents or added buffers. This product is intended for intravenous administration.

The formulas of the active ingredients are:

Ingredients | Molecular Formula | Molecular Weight
Sodium Acetate Trihydrate USP | CH3COONa•3H2O | 136.08
Potassium Chloride USP | KCl | 74.55
Magnesium Chloride Hexahydrate USP | MgCl2•6H2O | 203.30
Dibasic Potassium Phosphate USP | K2HPO4 | 174.18
Hydrous Dextrose USP |  | 198.17

Not made with natural rubber latex, PVC or DEHP.

The plastic container is made from a multilayered film specifically developed for parenteral drugs. It contains no plasticizers. The solution contact layer is a rubberized copolymer of ethylene and propylene. Solutions in contact with the plastic container may leach out certain chemical components from the plastic in very small amounts; however, biological testing was supportive of the safety of the plastic container materials. The container-solution unit is a closed system and is not dependent upon entry of external air during administration. The container is overwrapped to provide protection from the physical environment and to provide an additional moisture barrier when necessary. Exposure to temperatures above 25°C/77°F during transport and storage will lead to minor losses in moisture content. Higher temperatures lead to greater losses. It is unlikely that these minor losses will lead to clinically significant changes within the expiration period.

Addition of medication should be accomplished using complete aseptic technique.

The closure system has two ports; the one for the administration set has a tamper evident plastic protector and the other is a medication site. Refer to the Directions for Use of the container.

CLINICAL PHARMACOLOGY

Isolyte® P in 5% Dextrose provides electrolytes and calories, and is a source of water for hydration. It is capable of inducing diuresis depending on the clinical condition of the patient.

Sodium, the major cation of the extracellular fluid, functions primarily in the control of water distribution, fluid balance, and osmotic pressure of body fluids. Sodium is also associated with chloride and bicarbonate in the regulation of the acid-base equilibrium of body fluid.

Potassium, the principal cation of intracellular fluid, participates in carbohydrate utilization and protein synthesis, and is critical in the regulation of nerve conduction and muscle contraction, particularly in the heart.

Chloride, the major extracellular anion, closely follows the metabolism of sodium, and changes in the acid-base balance of the body are reflected by changes in the chloride concentration.

Magnesium, a principal cation of soft tissue, is primarily involved in enzyme activity associated with the metabolism of carbohydrates and protein. Magnesium is also involved in neuromuscular irritability.

Phosphate is a major intracellular anion which participates in providing energy for metabolism of substrates and contributes to significant metabolic and enzymatic reactions in almost all organs and tissues. It exerts a modifying influence on calcium levels, a buffering effect on acid-base equilibrium and has a primary role in the renal excretion of hydrogen ions.

Acetate is an organic ion which is a hydrogen ion acceptor and contributes bicarbonate during its metabolism to carbon dioxide and water, and in sufficient quantities may serve as an alkalinizing agent.

Dextrose provides a source of calories. Dextrose is readily metabolized, may decrease losses of body protein and nitrogen, promotes glycogen deposition and decreases or prevents ketosis if sufficient doses are provided.

INDICATIONS AND USAGE

This solution is indicated for use in adults as a source of electrolytes, calories and water for hydration, and as an alkalinizing agent.

CONTRAINDICATIONS

Solutions containing dextrose may be contraindicated in patients with hypersensitivity to corn products.

WARNINGS

The administration of intravenous solutions can cause fluid and/or solute overload resulting in dilution of serum electrolyte concentrations, overhydration, congested states or pulmonary edema. The risk of dilutional states is inversely proportional to the electrolyte concentration. The risk of solute overload causing congested states with peripheral and pulmonary edema is directly proportional to the electrolyte concentration.

Solutions containing sodium ions should be used with great care, if at all, in patients with congestive heart failure, severe renal insufficiency, and in clinical states in which there is sodium retention with edema.

Solutions containing potassium ions should be used with great care, if at all, in patients with hyperkalemia, severe renal failure, and in conditions in which potassium retention is present.

In patients with diminished renal function, administration of solutions containing sodium or potassium ions may result in sodium or potassium retention.

Infuse solutions containing phosphate slowly to avoid phosphate intoxication. Infusing high concentrations of phosphate may cause hypocalcemia and tetany. Serum phosphorus and calcium levels should be monitored frequently.

Solutions containing acetate should be used with great care in patients with metabolic or respiratory alkalosis. The administration of acetate should be done with great care in those conditions in which there is an increased level or an impaired utilization of acetate, such as severe hepatic insufficiency.

PRECAUTIONS

General

This solution should be used with care in patients with hypervolemia, renal insufficiency, urinary tract obstruction, impending or frank cardiac decompensation.

Extraordinary electrolyte losses such as may occur during protracted nasogastric suction, vomiting, diarrhea or gastrointestinal fistula drainage may necessitate additional electrolyte supplementation.

Additional essential electrolytes, minerals, and vitamins should be supplied as needed.

Care should be exercised in administering solutions containing sodium or potassium to patients with renal or cardiovascular insufficiency, with or without congestive heart failure, particularly if they are postoperative or elderly.

Potassium therapy should be guided primarily by serial electrocardiograms, especially in patients receiving digitalis. Serum potassium levels are not necessarily indicative of tissue potassium levels.

Solutions containing potassium or magnesium should be used with caution in the presence of cardiac disease, particularly in the presence of renal disease.

Solutions containing acetate should be used with caution. Excess administration may result in metabolic alkalosis.

Solutions containing dextrose should be used with caution in patients with overt or known subclinical diabetes mellitus, or carbohydrate intolerance for any reason.

To minimize the risk of possible incompatibilities arising from mixing this solution with other additives that may be prescribed, the final infusate should be inspected for cloudiness or precipitation immediately after mixing, prior to administration, and periodically during administration.

Do not use plastic containers in series connection.

If administration is controlled by a pumping device, care must be taken to discontinue pumping action before the container runs dry or air embolism may result. If administration is not controlled by a pumping device, refrain from applying excessive pressure (>300mmHg) causing distortion to the container such as wringing or twisting. Such handling could result in breakage of the container.

This solution is intended for intravenous administration using sterile equipment.

Use only if solution is clear and container and seals are intact.

Laboratory Tests

Clinical evaluation and periodic laboratory determinations are necessary to monitor changes in fluid balance, electrolyte concentrations, and acid-base balance during prolonged parenteral therapy or whenever the condition of the patient warrants such evaluation. Significant deviations from normal concentrations may require the use of additional electrolyte supplements, or the use of electrolyte-free dextrose solutions to which individualized electrolyte supplements may be added.

Drug Interactions

Sodium-containing solutions should be administered with caution to patients receiving corticosteroids or corticotropin, or to other salt-retaining patients.

Administration of barbiturates, narcotics, hypnotics, or systemic anesthetics should be adjusted with caution in patients also receiving magnesium-containing solutions because of an additive central depressive effect.

Parenteral magnesium should be administered with extreme caution to patients receiving digitalis preparations.

Carcinogenesis, mutagenesis, impairment of fertility

Long term animal studies with Isolyte® P (Multi-Electrolyte Injection) in 5% Dextrose have not been performed to evaluate the carcinogenic potential, mutagenic potential, or effects on fertility.

Pregnancy

Teratogenic Effects

Animal reproduction studies have not been conducted with Isolyte® P in 5% Dextrose. It is also not known whether Isolyte® P in 5% Dextrose can cause fetal harm when administered to a pregnant woman or can affect reproduction capacity. Isolyte® P in 5% Dextrose should be given to a pregnant woman only if clearly needed.

Labor and Delivery

As reported in the literature, Dextrose and electrolyte solutions have been administered during labor and delivery. Caution should be exercised, and the fluid balance, glucose and electrolyte concentrations, and acid-base balance, of both mother and fetus should be evaluated periodically or whenever warranted by the condition of the patient or fetus.

Nursing Mothers

Caution should be exercised when Isolyte® P in 5% Dextrose is administered to a nursing woman.

Pediatric Use

Safety and effectiveness in pediatric patients have not been established.

Geriatric Use

In general, dose selection for an elderly patient should be cautious, usually starting at the low end of the dosing range, reflecting the greater frequency of decreased hepatic, renal, or cardiac function, and of concomitant disease or other drug therapy.

This drug is known to be substantially excreted by the kidney, and the risk of toxic reactions to this drug may be greater in patients with impaired renal function. Because elderly patients are more likely to have decreased renal function, care should be taken in dose selection, and it may be useful to monitor renal function.

See WARNINGS.

ADVERSE REACTIONS

Reactions which may occur because of the solution or the technique of administration include febrile response, infection at the site of injection, venous thrombosis or phlebitis extending from the site of injection, extravasation and hypervolemia.

Too rapid infusion of hypertonic solutions may cause local pain and venous irritation. Rate of administration should be adjusted according to tolerance. Use of the largest peripheral vein and a small bore needle is recommended. (See DOSAGE AND ADMINISTRATION.)

Symptoms may result from an excess or deficit of one or more of the ions present in the solution; therefore, frequent monitoring of electrolyte levels is essential.

Hypernatremia may be associated with edema and exacerbation of congestive heart failure due to the retention of water, resulting in an expanded extracellular fluid volume.

Reactions reported with the use of potassium-containing solutions include nausea, vomiting, abdominal pain and diarrhea. The signs and symptoms of potassium intoxication include paresthesias of the extremities, areflexia, muscular or respiratory paralysis, mental confusion, weakness, hypotension, cardiac arrhythmias, heart block, electrocardiographic abnormalities and cardiac arrest. Potassium deficits result in disruption of neuromuscular function, and intestinal ileus and dilatation.

If infused in large amounts, chloride ions may cause a loss of bicarbonate ions, resulting in an acidifying effect.

Abnormally high plasma levels of magnesium can result in flushing, sweating, hypotension, circulatory collapse, and depression of cardiac and central nervous system function. Respiratory depression is the most immediate threat to life. Magnesium deficits can result in tachycardia, hypertension, hyperirritability and psychotic behavior.

Phosphorus deficiency may lead to impaired tissue oxygenation and acute hemolytic anemia. Relative to calcium, excessive phosphorus intake can precipitate hypocalcemia with cramps, tetany and muscular hyperexcitability.

The physician should also be alert to the possibility of adverse reactions to drug additives. Prescribing information for drug additives to be administered in this manner should be consulted.

If an adverse reaction does occur, discontinue the infusion, evaluate the patient, institute appropriate therapeutic countermeasures and save the remainder of the fluid for examination if deemed necessary.

OVERDOSAGE

In the event of a fluid or solute overload during parenteral therapy, reevaluate the patient's condition, and institute appropriate corrective treatment.

In the event of overdosage with potassium-containing solutions, discontinue the infusion immediately and institute corrective therapy to reduce serum potassium levels.

Treatment of hyperkalemia includes the following:

- Dextrose Injection USP, 10% or 25% containing 10 units of crystalline insulin per 20 grams of dextrose administered intravenously, 300 to 500 mL per hour.
- Absorption and exchange of potassium using sodium or ammonium cycle cation exchange resin, orally and as retention enema.
- Hemodialysis and peritoneal dialysis. The use of potassium-containing foods or medications must be eliminated. However, in cases of digitalization, too rapid a lowering of plasma potassium concentration can cause digitalis toxicity.

Over-aggressive phosphate replacement may precipitate hypocalcemic tetany. To prevent hypocalcemia, calcium supplementation should always accompany phosphate administration.

DOSAGE AND ADMINISTRATION

This solution is for intravenous use only.

Dosage is to be directed by a physician and is dependent upon age, weight, clinical condition of the patient and laboratory determinations. Frequent laboratory determinations and clinical evaluation are essential to monitor changes in blood glucose and electrolyte concentrations, and fluid and electrolyte balance during prolonged parenteral therapy.

When a hypertonic solution is to be administered peripherally, it should be slowly infused through a small bore needle, placed well within the lumen of a large vein to minimize venous irritation. Carefully avoid infiltration.

Fluid administration should be based on calculated maintenance or replacement fluid requirements for each patient.

Some additives may be incompatible. Consult with pharmacist. When introducing additives, use aseptic techniques. Mix thoroughly. Do not store.

Parenteral drug products should be inspected visually for particulate matter and discoloration prior to administration, whenever solution and container permit.

Directions for Use of EXCEL® Container

To Open

Tear overwrap down at notch and remove solution container. Check for minute leaks by squeezing solution container firmly. If leaks are found, discard solution as sterility may be impaired. If supplemental medication is desired, follow directions below before preparing for administration.

Before use, perform the following checks:

- Inspect each container. Read the label. Ensure solution is the one ordered and is within the expiration date.
- Invert container and carefully inspect the solution in good light for cloudiness, haze, or particulate matter. Any container which is suspect should not be used.
- Use only if solution is clear and container and seals are intact.

Preparation for Administration

1. Remove plastic protector from sterile set port at bottom of container.
2. Attach administration set. Refer to complete directions accompanying set.

To Add Medication Before Solution Administration

1. Prepare medication site.
2. Using syringe with 18–22 gauge needle, puncture medication port and inner diaphragm and inject.
3. Squeeze and tap ports while ports are upright and mix solution and medication thoroughly.

To Add Medication During Solution Administration

1. Close clamp on the set.
2. Prepare medication site.
3. Using syringe with 18–22 gauge needle of appropriate length (at least 5/8 inch), puncture resealable medication port and inner diaphragm and inject.
4. Remove container from IV pole and/or turn to an upright position.
5. Evacuate both ports by tapping and squeezing them while container is in the upright position.
6. Mix solution and medication thoroughly.
7. Return container to in use position and continue administration.

HOW SUPPLIED

Isolyte® P (Multi-Electrolyte Injection) in 5% Dextrose is supplied sterile and nonpyrogenic in EXCEL® containers. The 500 mL containers are packaged 24 per case.

NDC | REF | Size
Isolyte® P in 5% Dextrose
0264-7730-10 | L7301 | 500 mL

STORAGE AND HANDLING

Exposure of pharmaceutical products to heat should be minimized. Avoid excessive heat. Protect from freezing. It is recommended that the product be stored at room temperature (25°C).

Rx only

Revised: June 2018
EXCEL and Isolyte are registered trademarks of B. Braun Medical Inc.

B. Braun Medical Inc.
Bethlehem, PA 18018-3524 USA
1-800-227-2862

Y36-002-950 LD-499-2

PRINCIPAL DISPLAY PANEL - 500 mL Container Label

Isolyte® P in 5% Dextrose
(Multi-Electrolyte Injection)

REF L7301
NDC 0264-7730-10
HK 22411

500 mL
EXCEL® CONTAINER

Electrolytes (mEq/liter):

Na^+ 23
K^+ 20
Mg^++ 3
Cl^– 29
Acetate 23
Phosphate
(HPO) 3
(1.5 mmole P/L)

Each 100 mL contains: Hydrous Dextrose USP 5 g; Sodium Acetate•3H2O USP
0.32 g; Potassium Chloride USP 0.13 g; Magnesium Chloride•6H2O USP 0.031 g;
Dibasic Potassium Phosphate USP 0.026 g; Water for Injection USP qs
pH adjusted with HCl NF
pH: 5.0 (4.0-6.0) Calc Osmolarity: 340 mOsmol/liter

Sterile, nonpyrogenic. Single dose container. Do not use in series connection. For
intravenous use only.Use only if solution is clear and container and seals are intact.

WARNINGS: Some additives may be incompatible. Consult with pharmacist. When
introducing additives, use aseptic techniques. Mix thoroughly. Do not store.

Recommended Storage: Room temperature (25°C). Avoid excessive heat. Protect
from freezing. See Package Insert.

Do not remove overwrap until ready for use. After removing the overwrap, check for minute leaks by squeezing container firmly. If leaks are found, discard solution as sterility may be impaired.
Not made with natural rubber latex, PVC or DEHP.

Rx only

EXCEL and Isolyte are registered trademarks of B. Braun Medical Inc.

B. Braun Medical Inc.
Bethlehem, PA 18018 3524 USA
1-800-227-2862

Y94-003-244
LD-145-4

EXP
LOT